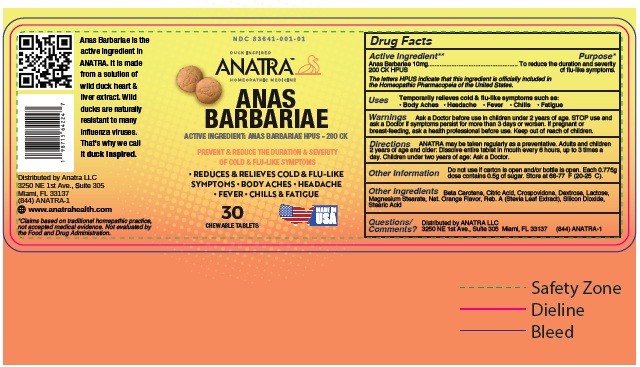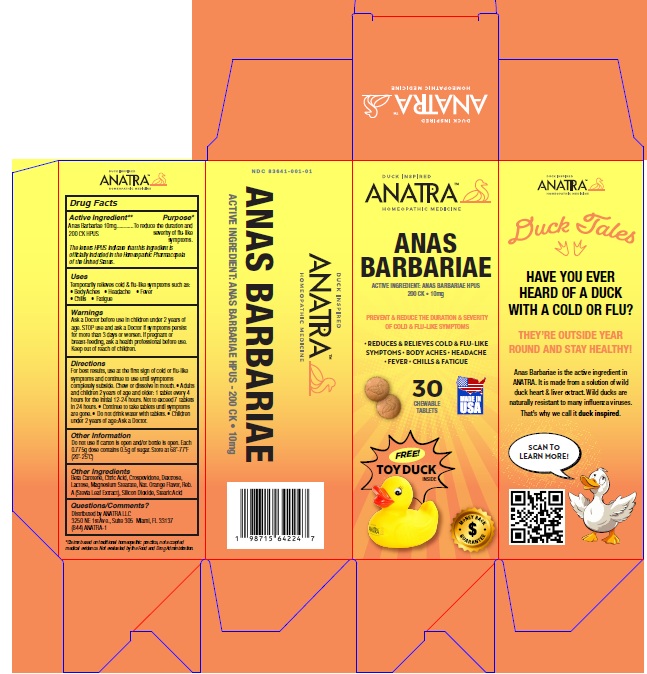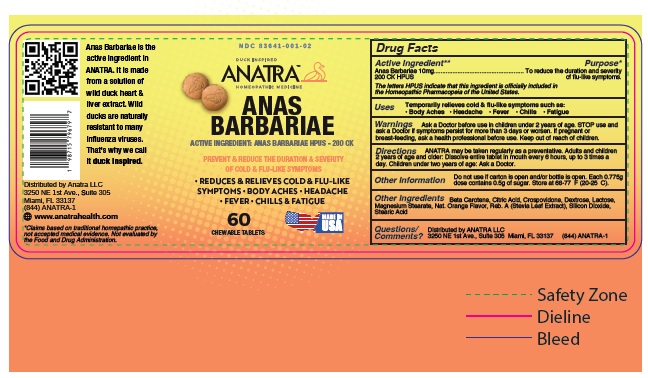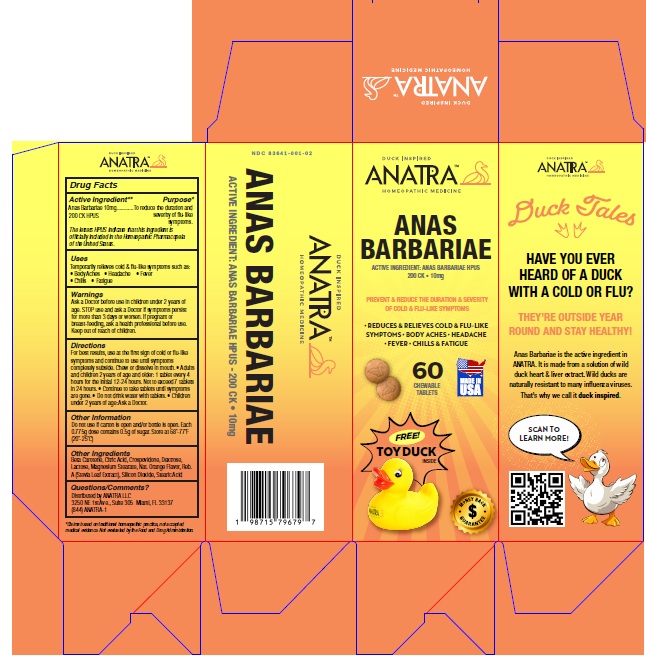 DRUG LABEL: Anatra
NDC: 83641-001 | Form: TABLET
Manufacturer: Anatra LLC
Category: otc | Type: HUMAN OTC DRUG LABEL
Date: 20251007

ACTIVE INGREDIENTS: CAIRINA MOSCHATA HEART/LIVER AUTOLYSATE 200 [hp_C]/1 1
INACTIVE INGREDIENTS: BETA CAROTENE; CITRIC ACID MONOHYDRATE; CROSPOVIDONE, UNSPECIFIED; DEXTROSE, UNSPECIFIED FORM; LACTOSE, UNSPECIFIED FORM; MAGNESIUM STEARATE; REBAUDIOSIDE A; SILICON DIOXIDE; STEARIC ACID

Active Ingredient

Anas barbariae. HPUS - 200 CK

Purpose

To reduce the duration and severity of cold & flu-like symptoms. The letters HPUS indicate that this ingredient is officially included in the Homeopathic Pharmacopeia of the United States.

Uses

Temporarily relieves cold & flu-like symptoms such as:

- Body aches
- Headache
- Fever
- Chills
- Fatigue

Warnings

Ask a Doctor before usein children under 2 years of age.
Stop use and ask a Doctor if symptoms persist for more than 3 days or worsen.
If pregnant or breast-feeding, ask a health professional before use.
Keep out of reach of children.

Directions

ANATRA may be taken regularly as a preventative.
Adults and children 2 years of age and older: Dissolve entire tablet in mouth every
6 hours, up to 3 times a day. Children under two years of age: Ask a Doctor.

Other Information

Do not use if carton is open and/or bottle is open.Each 0.775g dose contains 0.5g of sugar. Store at 68-77°F (20-25°C).

Inactive ingredients

Beta Carotene, Citric Acid, Crospovidone, Dextrose,Lactose, Magnesium Stearate, Nat. Orange Flavor, Reb. A (Stevia LeafExtract), Silicon Dioxide, Stearic Acid

Questions/Comments?

Distributed by Anatra LLC 3250 NE 1st Ave., Suite 305 Miami, FL 33137 (844) ANATRA-1